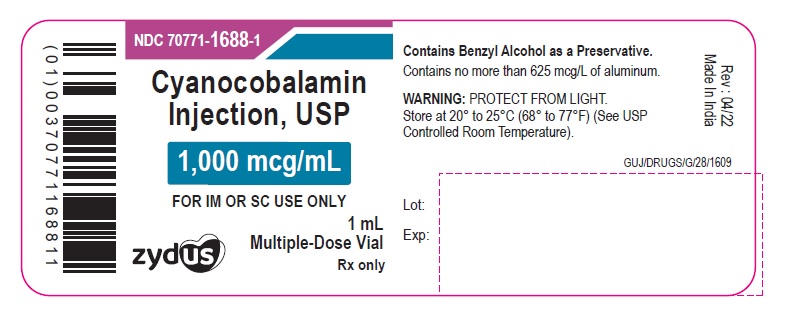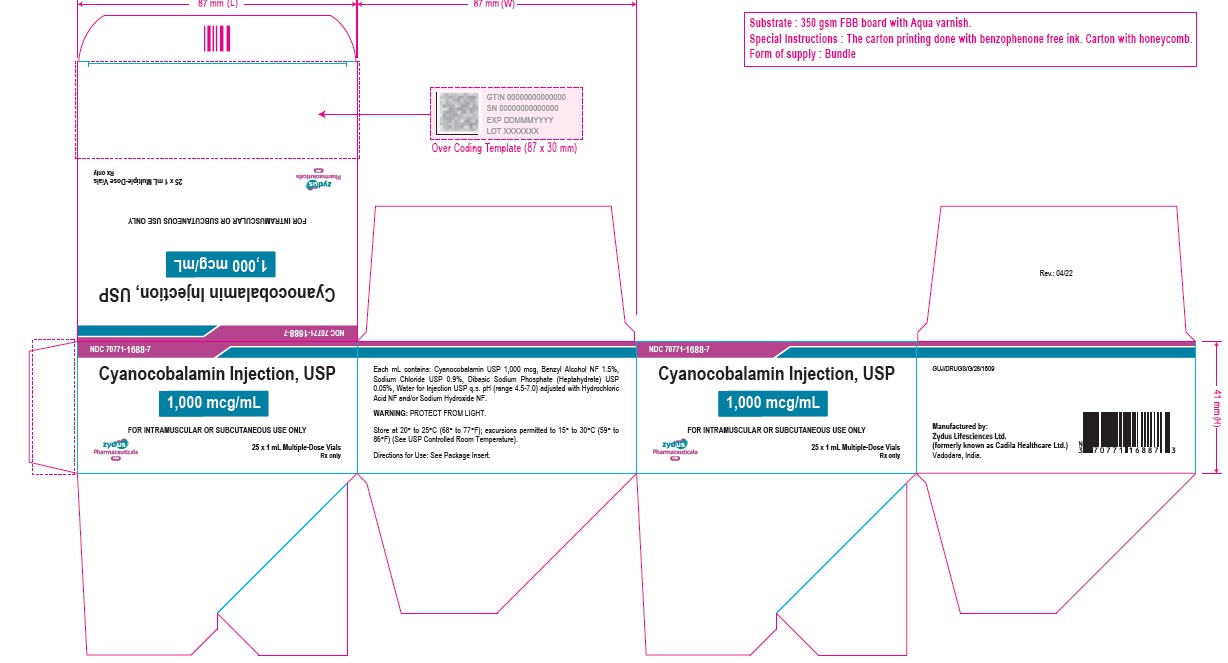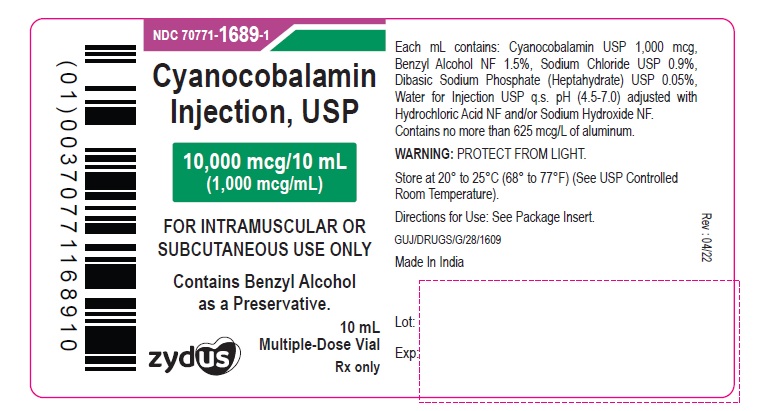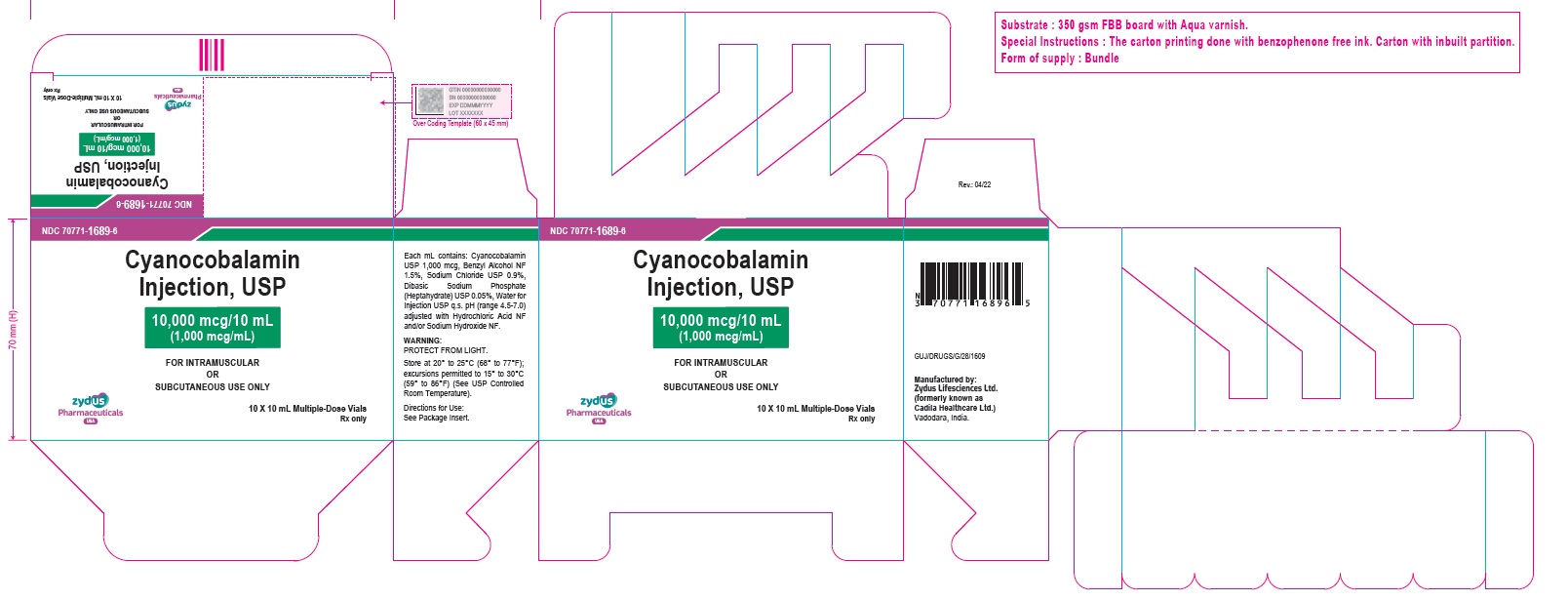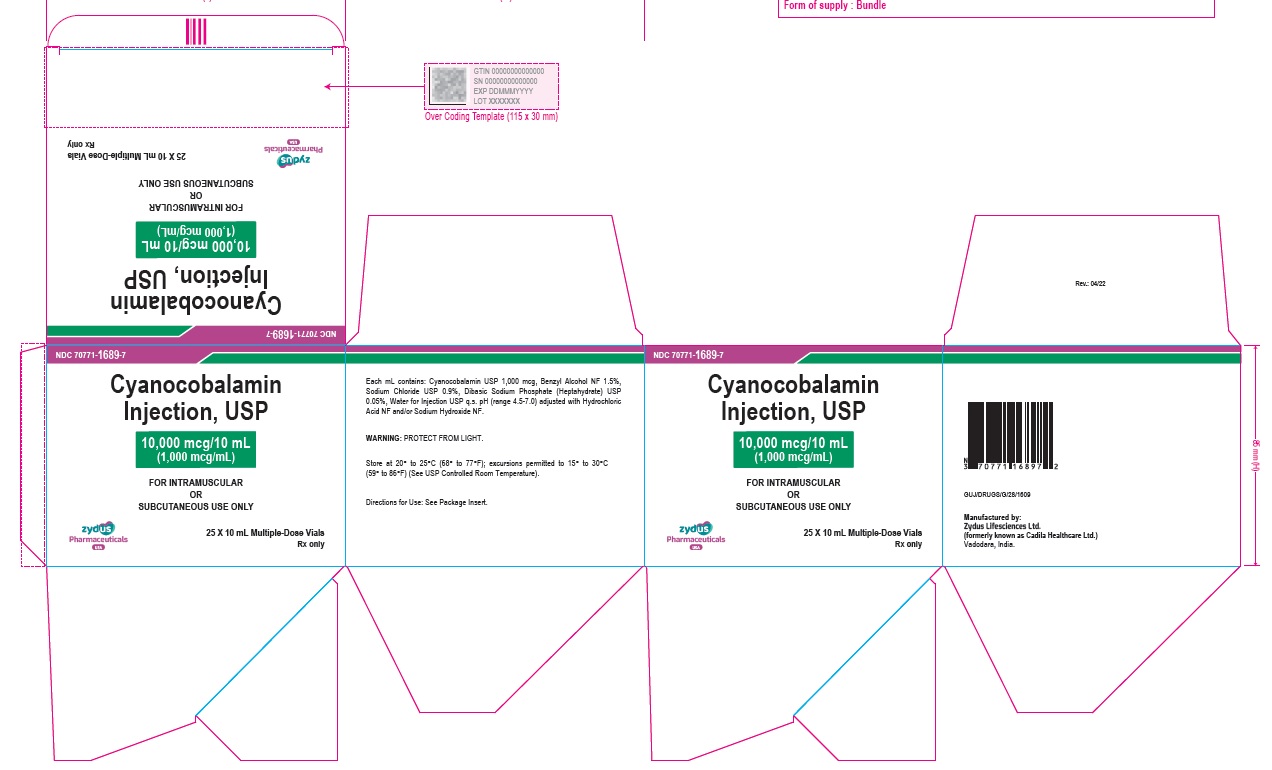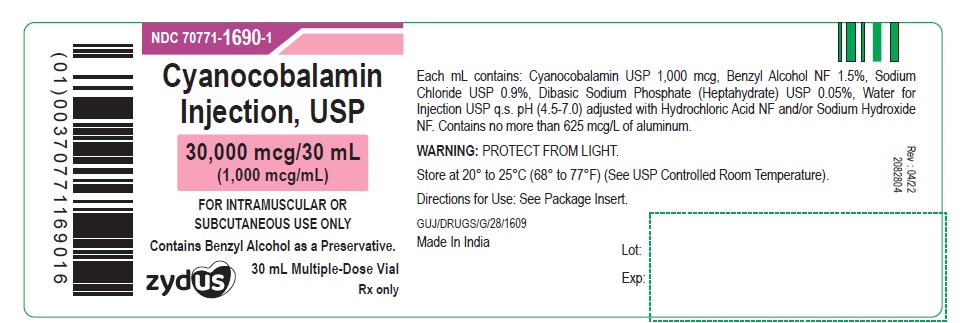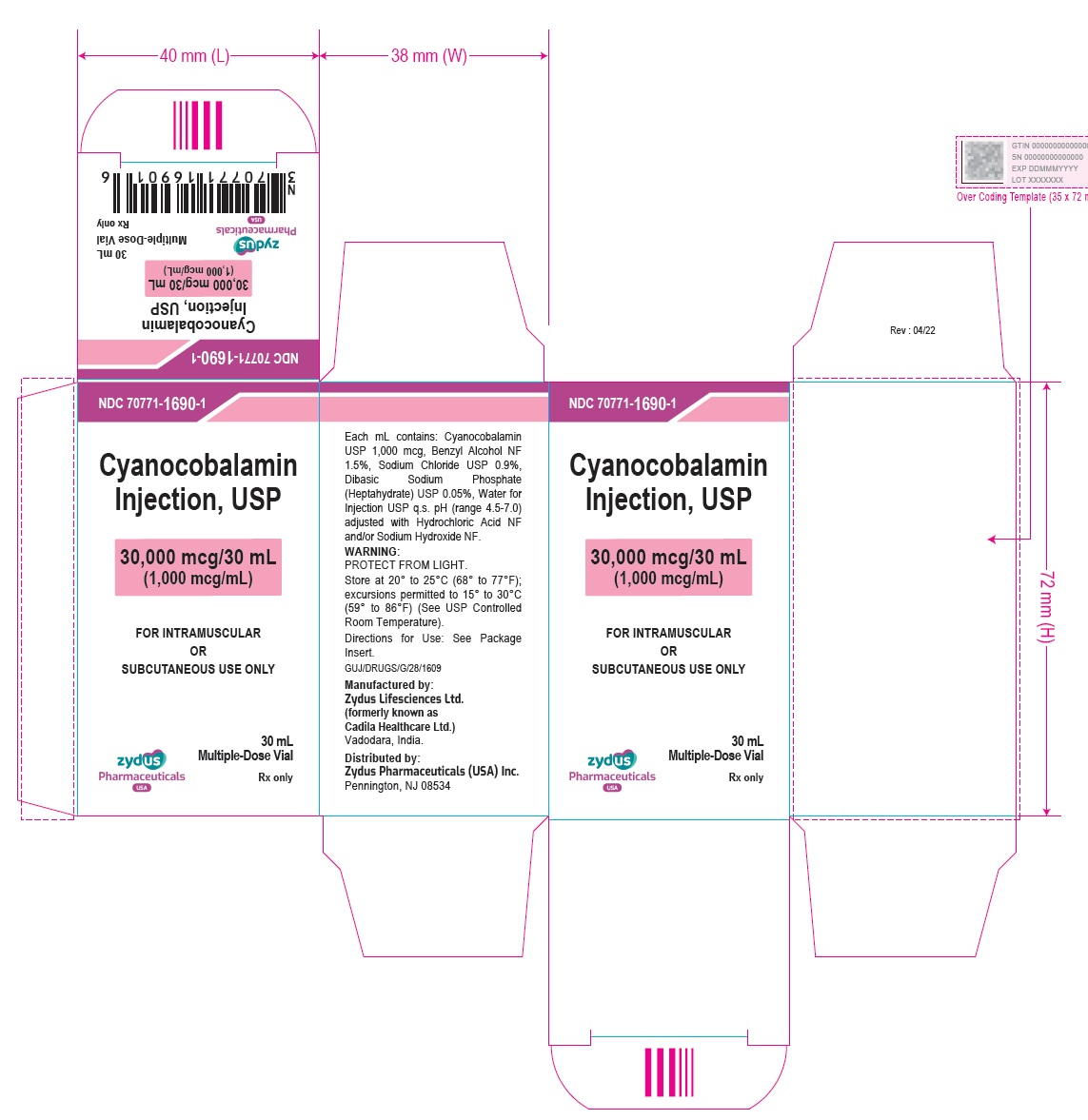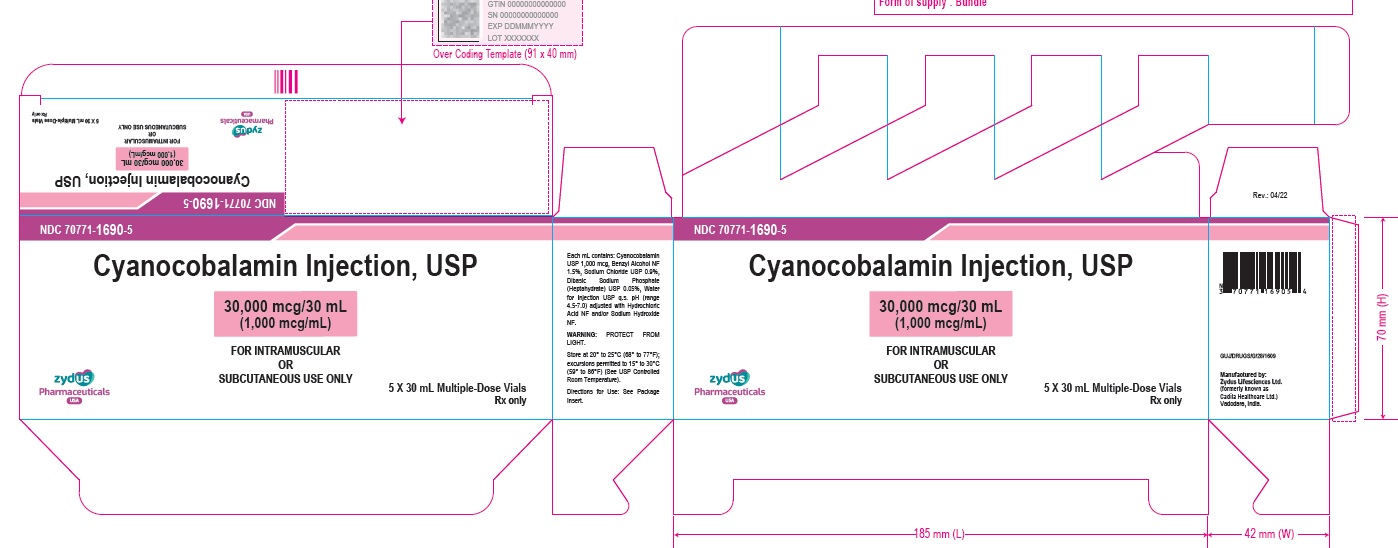 DRUG LABEL: cyanocobalamin
NDC: 70771-1688 | Form: INJECTION, SOLUTION
Manufacturer: Zydus Lifesciences Limited
Category: prescription | Type: HUMAN PRESCRIPTION DRUG LABEL
Date: 20220419

ACTIVE INGREDIENTS: CYANOCOBALAMIN 1000 ug/1 mL
INACTIVE INGREDIENTS: SODIUM CHLORIDE; BENZYL ALCOHOL; SODIUM PHOSPHATE, DIBASIC, HEPTAHYDRATE; HYDROCHLORIC ACID; SODIUM HYDROXIDE; WATER

Cyanocobalamin Injection, USP

PACKAGE LABEL.PRINCIPAL DISPLAY PANEL

NDC 70771-1688-1

Cyanocobalamin Injection, USP

1,000 mcg/mL

FOR IM OR SC USE ONLY

1 mL Multiple-dose Vial

Rx only

NDC 70771-1668-7

Cyanocobalamin Injection, USP

1,000 mcg/mL

FOR INTRAMUSCULAR OR SUBCUTANEOUS USE ONLY

25 X 1 mL Multiple-dose Vials

Rx only

NDC 70771-1689-1

Cyanocobalamin Injection, USP

10,000 mcg/10 mL (1,000 mcg/mL)

FOR INTRAMUSCULAR OR SUBCUTANEOUS USE ONLY

Contains Benzyl Alcohol as a Preservative.

10 mL Multiple-Dose Vial

Rx only

NDC 70771-1689-6

Cyanocobalamin Injection, USP

10,000 mcg/10 mL (1,000 mcg/mL)

FOR INTRAMUSCULAR OR SUBCUTANEOUS USE ONLY

10 X 10 mL Multiple-Dose Vials

Rx only

NDC 70771-1689-7

Cyanocobalamin Injection, USP

10,000 mcg/10 mL (1,000 mcg/mL)

FOR INTRAMUSCULAR OR SUBCUTANEOUS USE ONLY

25 X 10 mL Multiple-Dose Vials

Rx only

NDC 70771-1690-1

Cyanocobalamin Injection, USP

30,000 mcg/30 mL (1,000 mcg/mL)

FOR INTRAMUSCULAR OR SUBCUTANEOUS USE ONLY

Contains Benzyl Alcohol as a Preservative.

30 mL Multiple-Dose Vial

Rx only

NDC 70771-1690-1

Cyanocobalamin Injection, USP

30,000 mcg/30 mL (1,000 mcg/mL)

FOR INTRAMUSCULAR OR SUBCUTANEOUS USE ONLY

30 mL Multiple-Dose Vial – Carton Label

Rx only

NDC 70771-1690-5

Cyanocobalamin Injection, USP

30,000 mcg/30 mL (1,000 mcg/mL)

FOR INTRAMUSCULAR OR SUBCUTANEOUS USE ONLY

5 X 30 mL Multiple-Dose Vials

Rx only